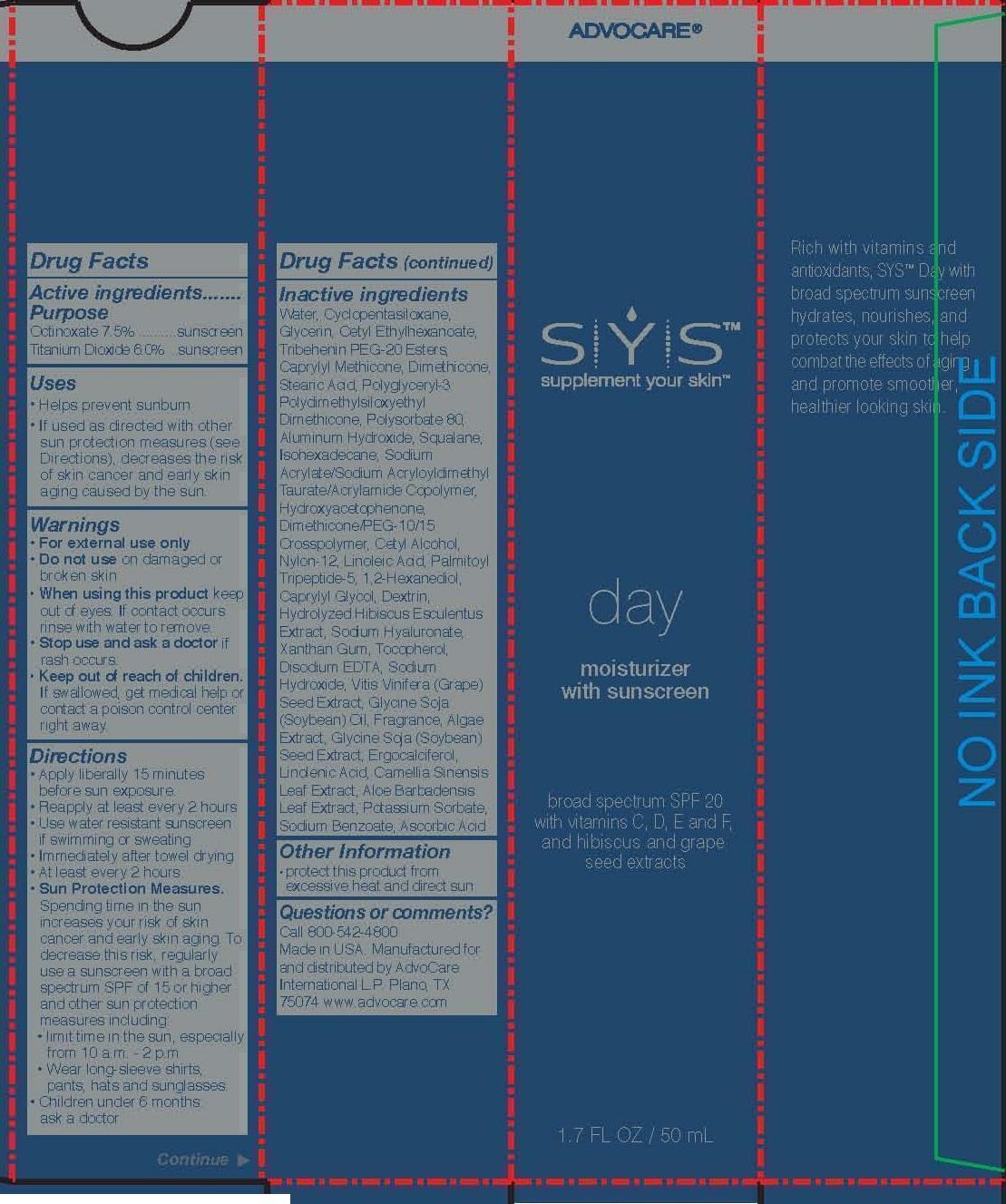 DRUG LABEL: SYS
NDC: 68990-001 | Form: LOTION
Manufacturer: AdvoCare International L.P.
Category: otc | Type: HUMAN OTC DRUG LABEL
Date: 20140618

ACTIVE INGREDIENTS: OCTINOXATE 3.75 g/50 mL; TITANIUM DIOXIDE 3 g/50 mL
INACTIVE INGREDIENTS: WATER; CYCLOMETHICONE 5; GLYCERIN; CETYL ETHYLHEXANOATE; TRIBEHENIN PEG-20 ESTERS; DIMETHICONE; STEARIC ACID; POLYSORBATE 80; ALUMINUM HYDROXIDE; SQUALANE; ISOHEXADECANE; SODIUM ACRYLATE/SODIUM ACRYLOYLDIMETHYLTAURATE COPOLYMER (4000000 MW); 4-HYDROXY ACETOPHENONE; NYLON-12; LINOLEIC ACID; PALMITOYL TRIPEPTIDE-5; 1,2-HEXANEDIOL; CAPRYLYL GLYCOL; CETYL ALCOHOL; ICODEXTRIN; HYALURONATE SODIUM; XANTHAN GUM; TOCOPHEROL; EDETATE DISODIUM; SODIUM HYDROXIDE; VITIS VINIFERA SEED; SOYBEAN OIL; SOYBEAN; ERGOCALCIFEROL; LINOLENIC ACID; GREEN TEA LEAF; ALOE VERA LEAF; POTASSIUM SORBATE; SODIUM BENZOATE; ASCORBIC ACID

SYS
Drug Facts

Active Ingredients

Octinoxate 7.5%

Titanium Dioxide 6.0%

Purpose

Sunscreen

Uses

- Helps prevent sunburn
- If used as directed with other sun protection measures (see Direction), decreases the risk of skin cancer and early skin aging caused by the sun.

Warnings

For external use only

Do not use on damaged or broken skin

When using this product keep out of eyes. If contact occures rinse with water to remove.

Stop use and ask a doctor if rash occurs.

Keep out of reach of children. If swallowed, get medical help or contact a poison control center right away.

Directions

- Apply liberally 15 minutes before sun exposure.
- Reapply at least every 2 hours
- Use water resistant sunscreen if swimming or sweating
- Immediately after towel drying
- At least every 2 hours
- Sun Protection Measures.

Spending time in the sun increases your risk of skin cancer and early skin aging. To decrease this risk, regularly use a sunscreen with a broad spectrum SPF of 15 or higher and other sun protection measures including:

- limit time in the sun, especially from 10 a.m. - 2 p.m.
- Wear long-sleeve shirts, pants, hats and sunglasses.
- Children under 6 months ask a doctor

Inactive ingredients

water, cyclopentasiloxane, glycerin, cetyl ethylhexanoate, tribehenin PEG-20 esters, caprylyl methicone, dimethicone, stearic acid, polyglyceryl-3 polydimethylsiloxyethyl dimethicone, polysorbate 80, aluminum hydroxide, squalane, isohexadecane, sodium acrylate/sodium acryloyldimehtyl taurate/acrylamide copolymer, hydroxyacetophenone, dimethicone/PEG-10/15 corosspolymer, cetyl alcohol, nylon-12, linoleic acid, palmitoyl tripeptide-5, 1,2-hexanediol, caprylyl glycol, dextrin, hydrolyzed hibiscus esculentus extract, sodium hyaluronate, xanthan gum, tocopherol, disodium EDTA, sodium hydroxide, vitis vinifera (grape) seed extract, glycine soja (Soybean) oil, fragrance, algae extract, glycine soja (soybean) seed extract, ergocalciferol, linolenic acid, camellia sinensis leaf extract, aloe barbadensis leaf extract, potassium sorbate, sodium benzoate, ascorbic acid

Other Information

- protect this product from excessive heat and direct sun

Questions or comments?

Call 800-542-4800

Made in USA. Manufactured for and distributed by AdvoCare International L.P. Plano, TX 75074 www.advocare.com

Principal Display

SYS

supplement your skin

day

moisturizer

with sunscreen

broad specturm SPF 20

with vitamins C, D, E and F

and hibiscus and grape seed extracts